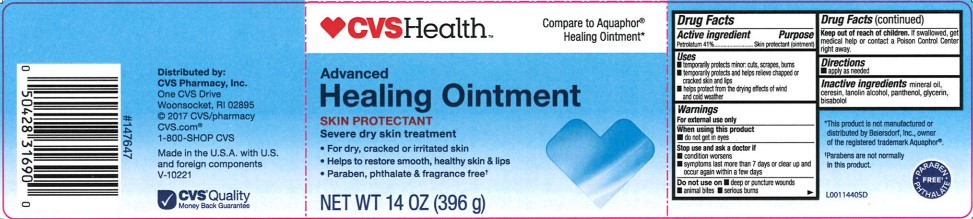 DRUG LABEL: Advanced Healing
NDC: 59779-086 | Form: OINTMENT
Manufacturer: CVS Pharamacy, Inc
Category: otc | Type: HUMAN OTC DRUG LABEL
Date: 20260202

ACTIVE INGREDIENTS: PETROLATUM 410 mg/1 g
INACTIVE INGREDIENTS: MINERAL OIL; CERESIN; LANOLIN ALCOHOLS; PANTHENOL; GLYCERIN; LEVOMENOL

CVS 247.000/247AA-AC
Healing Ointment for Dry and Cracked Skin

Active ingredient

Petrolatum 41%

Purpose

Skin protectant (ointment)

Uses

- temporarily protects minor: cuts, scrapes, burns
- temporarily protects and helps relieve chapped and cracked skin and lips
- helps protect from the drying effects of wind and cold weather

Warnings

For external use only

When using this product

- do not get in eyes

Stop use and ask a doctor if

- condition worsens
- symptoms last more than 7 days or clear up and occur again within a few days

Do not use on

- deep or puncture wounds
- animal bites
- serious burns

Keep out of reach of children.

If swallowed get medical help or contract a Poison Control Center right away.

Directions

- apply as needed

Inactive ingredients

minerol oil, ceresin, lanolin alcohol, panthenol, glycerin, bisabolol

Disclaimer

*This product is not manufactured or distributed by Beiersdorf Inc., owner of the registered trademark Aquaphor®.

Parabens are not normally in this product.

PARABEN / PHTHALATE FREE

Adverse Reactions

Distributed by:

CVS Pharmacy, Inc.

One CVS Drive

Woonsocket, RI 02895

(C) 2017 CVS/pharmacy

CVS.com

1-800-SHOP CVS

Made in the U.S.A. with U.S. and Foreign components

CVS Quality Money Back Guarantee

Principal display panel

CVS Health™

Compare to Aquaphor®Healing Ointment*

Advanced

Healing Ointment

SKIN PROTECTANT

Severe dry skin treatment

- For dry, cracked or irritated skin
- Helps to restore smooth, healthy skin and lips
- Paraben, phthalate & fragrance free†

NET WT 14 OZ (369 g)